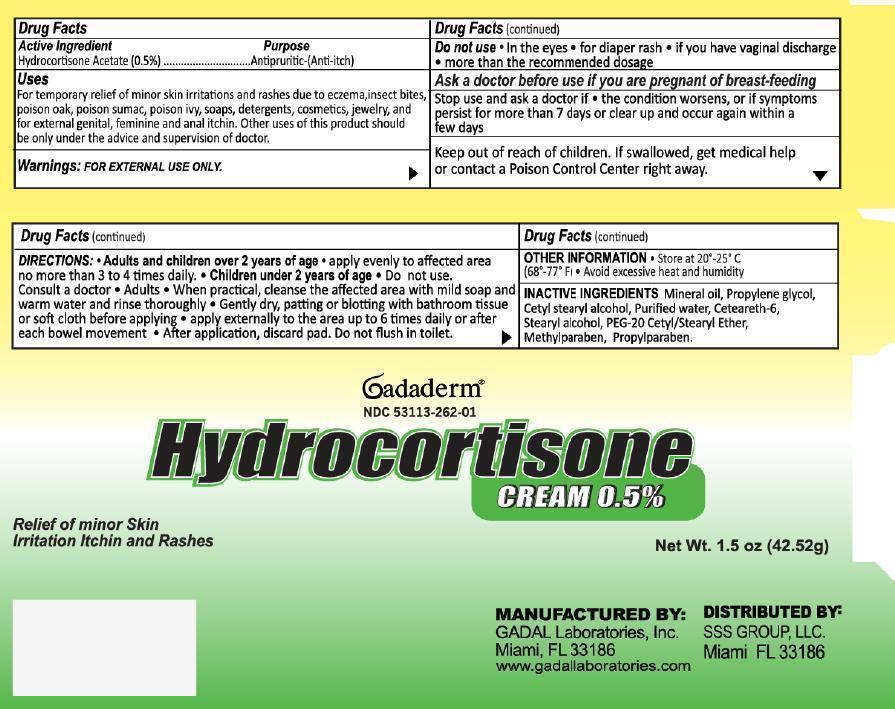 DRUG LABEL: Gadaderm Hydrocortisone
NDC: 53113-262 | Form: CREAM
Manufacturer: Gadal Laboratories Inc
Category: otc | Type: HUMAN OTC DRUG LABEL
Date: 20130905

ACTIVE INGREDIENTS: HYDROCORTISONE ACETATE 0.5 g/100 g
INACTIVE INGREDIENTS: MINERAL OIL; PROPYLENE GLYCOL; CETOSTEARYL ALCOHOL; WATER; CETEARETH-6; STEARYL ALCOHOL; POLYOXYL 20 CETOSTEARYL ETHER; METHYLPARABEN; PROPYLPARABEN

Active Ingredient Purpose

Hydrocortisone Acetate (0.5%) Antiruritic (Anti-itch)

Purpose

Antipruritic (Anti-itch)

Uses

For temporary relief of minor skin irritations and rashes due to eczema, insect bites, poison oak, poison sumac, poison ivy, soaps, detergents, cosmetics, jewelry, and for external genital, feminine and anal itchin. Other uses of this product should be only under the advice and supervision of doctor.

Warnings: For External Use Only.

Do not use

- in the eyes
- for diaper rash
- if you have vaginal discharge
- more than recommended dosage

Stop use and ask a doctor if

- the condition worsens, or if symptoms persist for more than 7 days or clear up and occur again within a few days

Ask a doctor before use if you are pregnant or breast-feeding

Keep out of reach of children. If swallowed, get medical help or contact a Poison Control Center right away

Directions

- Adults and children over 2 years of age: apply evenly to affected area no more than 3 to 4 times daily
- Children under 2 years of age: Do not use. Consult a doctor

Adults: When practical, cleanse the affected area with mild soap and warm water and rinse thoroughly. Gently dry, patting or blotting with bathroom tissue or soft cloth before applying. Apply externally to the area up to 6 times daily or after each bowel movement. After application, discard pad. Do not flush in toilet.

INACTIVE INGREDIENT

Inactive ingredients Mineral oil, propylene glycol, cety stearyl alcohol, purified water, ceteareth-6, stearyl alcohol, PEG-20 cetyl/stearyl ether, methylparaben, propylparaben

QUESTIONS

GADAL Laboratories, Inc.

Miami, Fl 33186

www.gadallaboratories.com